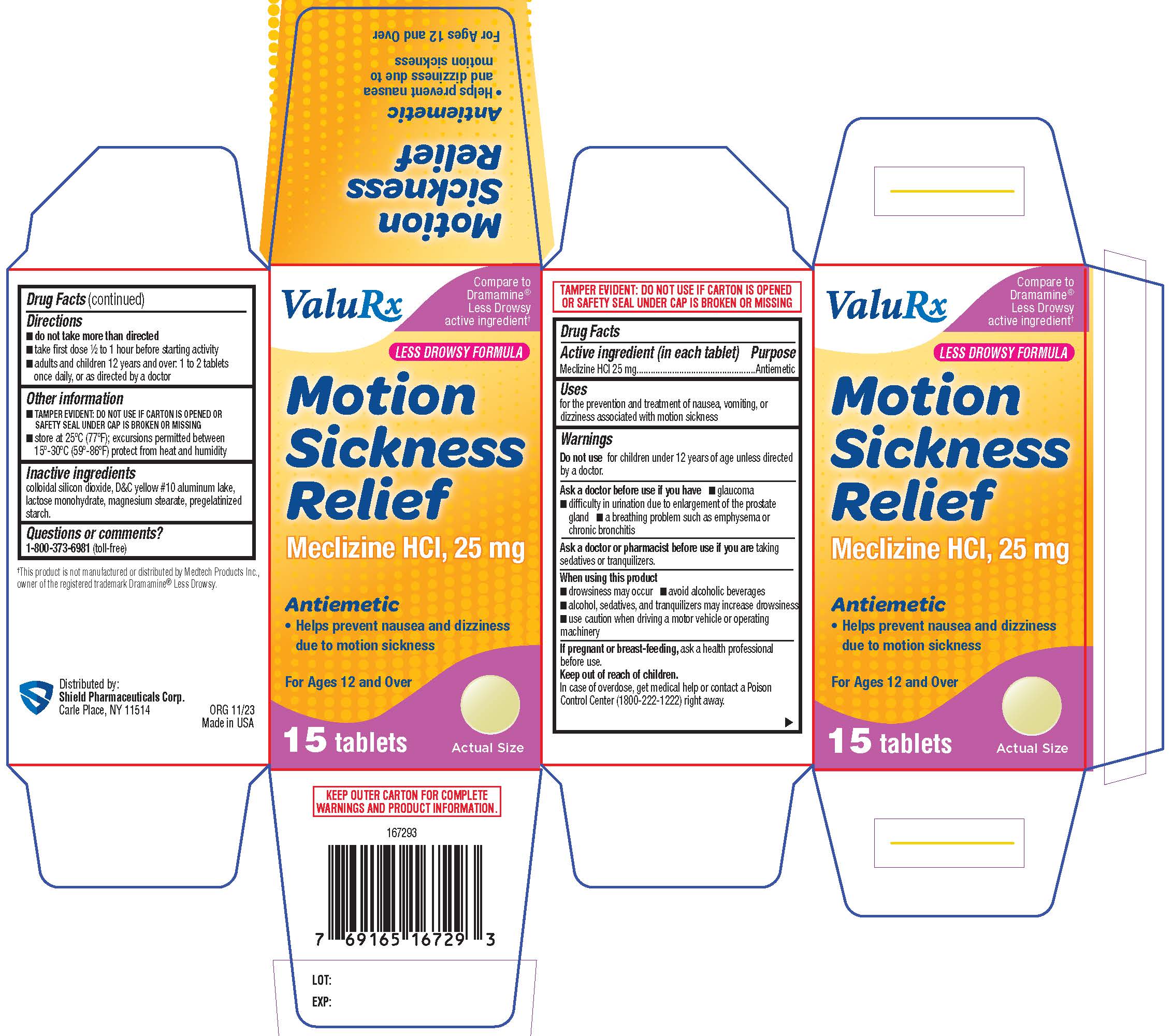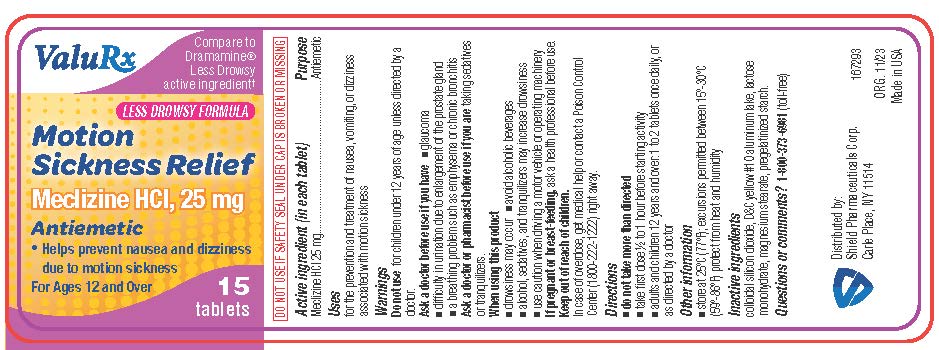 DRUG LABEL: Motion Sickness Relief
NDC: 83059-0007 | Form: TABLET, FILM COATED
Manufacturer: Shield Pharmaceuticals Corp
Category: otc | Type: HUMAN OTC DRUG LABEL
Date: 20251209

ACTIVE INGREDIENTS: MECLIZINE HYDROCHLORIDE 25 mg/1 1
INACTIVE INGREDIENTS: SILICON DIOXIDE; D&C YELLOW NO. 10 ALUMINUM LAKE; LACTOSE MONOHYDRATE; MAGNESIUM STEARATE; STARCH, CORN

Motion Sickness Relief

Drug Facts

Active ingredient (in each liquid-filled capsule)

Meclizine HCl 25 mg

Purpose

Antiemetic

Uses

for the prevention and treatment of nausea, vomiting, or dizziness associated with motion sickness

Warnings

Do not usefor children under 12 years of age unless directed by a doctor.

Ask a doctor before use if you have

- glaucoma
- difficulty in urination due to enlargement of the prostate gland
- a breathing problem such as emphysema or chronic bronchitis

Ask a doctor or pharmacist before use if you are

taking sedatives or tranquilizers.

When using this product

- drowsiness may occur n avoid alcoholic beverages
- alcohol, sedatives, and tranquilizers may increase drowsiness
- use caution when driving a motor vehicle or operating machinery

PREGNANCY OR BREAST FEEDING

If pregnant or breast-feeding, ask a health professional before use.

Keep out of reach of children. In case of overdose, get medical help or contact a Poison Control Center right away.1(800)222-1222

Directions

- do not take more than directed
- take first dose ½ to 1 hour before starting activity
- adults and children 12 years and over: 1 to 2 tablets once daily, or as directed by a doctor

Other information

- TAMPER EVIDENT: DO NOT USE IF CARTON IS OPENED OR SAFETY SEAL UNDER CAP IS BROKEN OR MISSING
- store at 25ºC (77ºF); excursions permitted between 15º-30ºC (59º-86ºF) protect from heat and humidity

Inactive ingredients

colloidal silicon dioxide, D&C yellow #10 aluminum lake, lactose monohydrate, magnesium stearate, pregelatinized starch.

Questions or comments?

1-800-373-6981 (toll-free)

Shield Pharmaceuticals Corp.
Ronkonkoma, NY 11779

PRINCIPAL DISPLAY PANEL

Compare to Dramamine® Less Drowsy active ingredient†

LESS DROWSY FORMULA

Motion Sickness Relief

Meclizine HCl, 25 mg

Antiemetic
Helps prevent nausea and dizziness due to motion sickness

For Ages 12 and Over